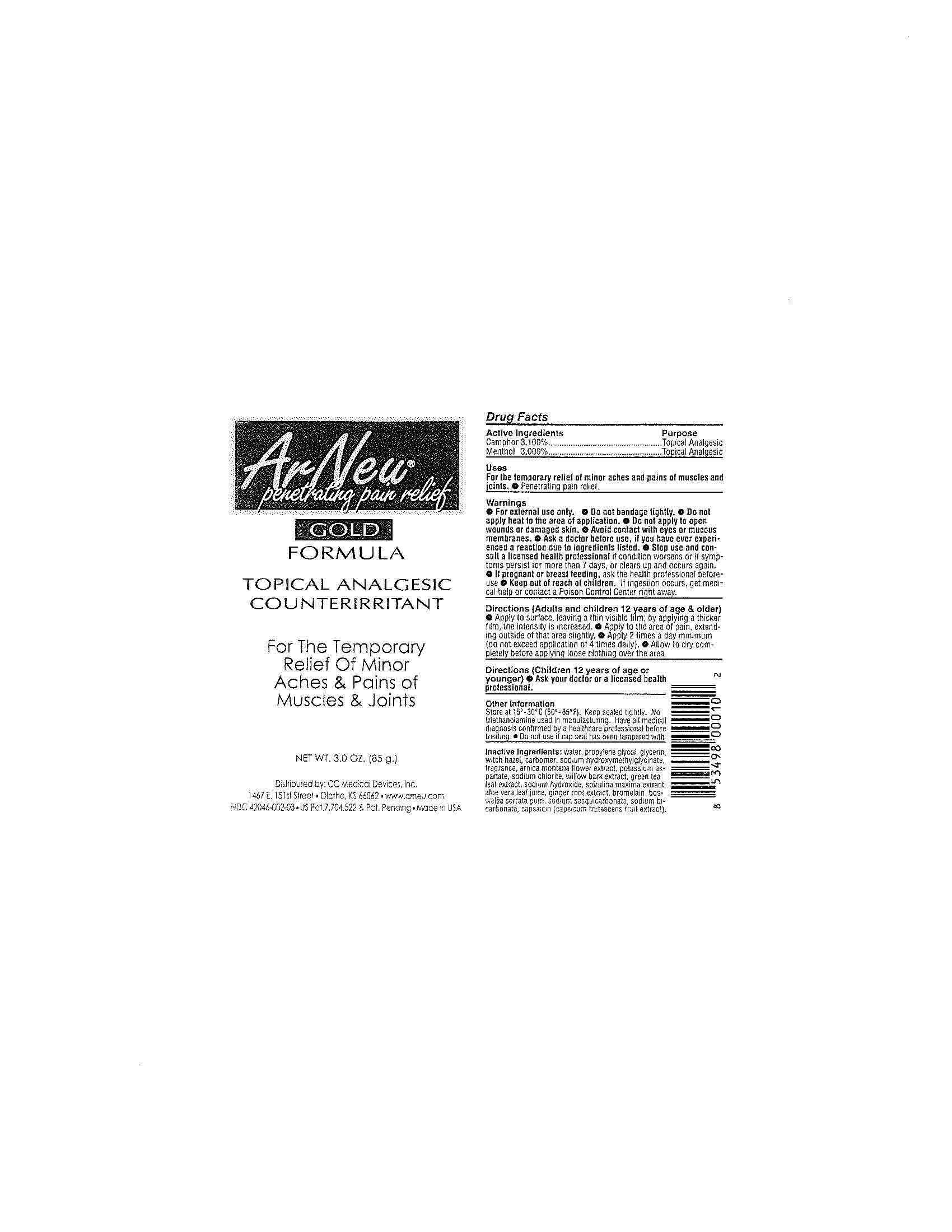 DRUG LABEL: Arneu
NDC: 42046-002 | Form: CREAM
Manufacturer: CC Medical Devices Inc
Category: otc | Type: HUMAN OTC DRUG LABEL
Date: 20100828

ACTIVE INGREDIENTS: Camphor (Natural) 3.1 g/100 g; Menthol 3.0 g/100 g
INACTIVE INGREDIENTS: Water; Propylene Glycol; Glycerin; Witch Hazel; Arnica Montana Flower; Potassium Aspartate; Sodium Chlorite; Willow Bark; Green Tea Leaf; Sodium Hydroxide; Aloe Vera Leaf; Ginger; Bromelains; Sodium Bicarbonate; Capsaicin

Drug Facts

Active Ingredients

Camphor 3.100%

Menthol 3.000%

Purpose

Topical Analgesic

Topical Analgesic

Uses

For the temporary relief of minor aches and pains of muscles and joints.

Penetrating pain relief.

Warnings

For external use only.

Do not bandage tightly.

Do not apply heat to the area of application.

Do not apply to open wounds or damaged skin.

WHEN USING

Avoid contact with eyes or mucous membranes.

Ask a doctor before use, if you have ever experienced a reaction due to ingredients listed.

Stop use and consult a licensed health professional if conditions worsens or if symptoms persists for more than 7 days, or clears up and occurs again.

PREGNANCY OR BREAST FEEDING

If pregnant or breast feeding, ask the health professional before use.

Keep out of reach of children.

If ingestion occurs, get medical help or contact a Poison Control Center right away.

Directions

Adults and children 12 years of age or older

Apply to surface, leaving a thin visible film; by applying a thicker film, the intensity is increased.

Apply to the area of pain, extending outside of the area slightly.

Apply 2 times a day minimum (do not exceed application of 4 times daily).

Allow to dry completely before applying loose clothing over the area.

Directions

(Children 12 years of age or younger)

Ask your doctor or a licensed health professional.

Other Information

Store at 15-30 C (50-85 F). Keep sealed tightly.

No triethanolamine used in manufacturing.

Have all medical diagnosis confirmed by a healthcare professional before treating.

Do not use if cap seal has been tampered with.

Inactive Ingredients

Water, propylene glycol, glycerin, witch hazel, carbomer, sodium hydroxymethylglycinate, fragrance, arnica montana flower extract, potassium asparate, sodium chlorite, willow bark extract, green tea leaf extract, sodium hydroxide, spirulina maxima extract, aloe vera leaf juice, ginger root extract, bromelain, boswellia serrata gum, sodium sesquicarbonate, sodium bicarbonate, capsaicin (capsicum frutescens fruit extract).

PACKAGE LABEL

ArNeu

penetrating pain relief

God Formula

Topical Analgesic Counterirritant

For the Temporary Relief of Minor Aches and Pains of Muscles and Joints

NET WT. 3.0 OZ. (85 g.)

www.arneu.com

NDC 42046-002-03

US Pat.7,704,522 and Pat. Pending

Made in USA